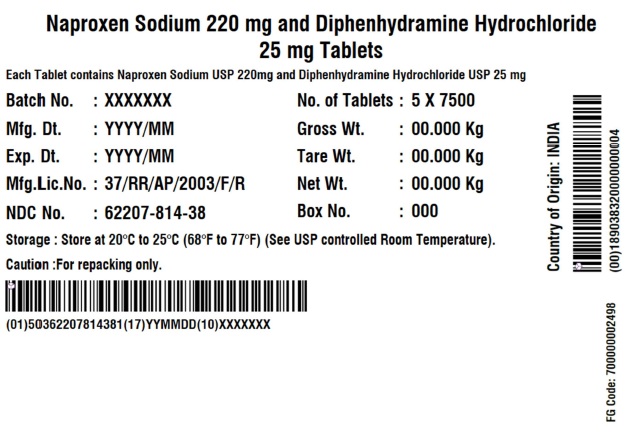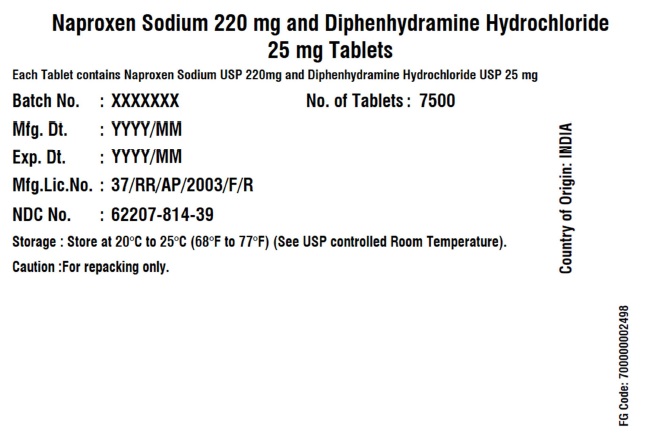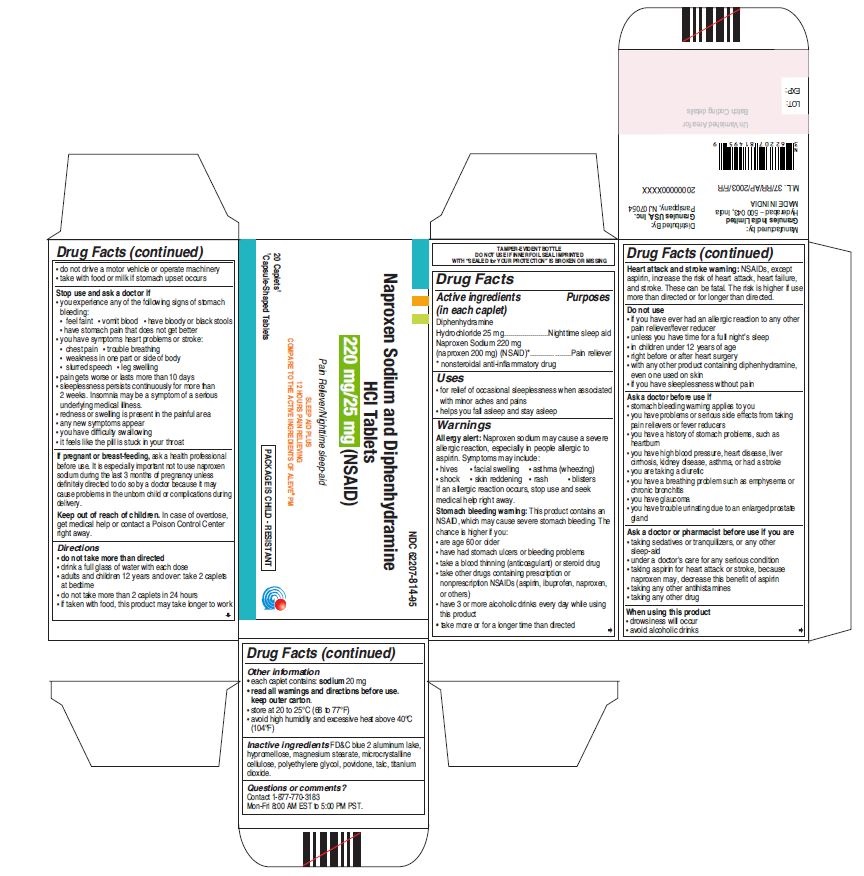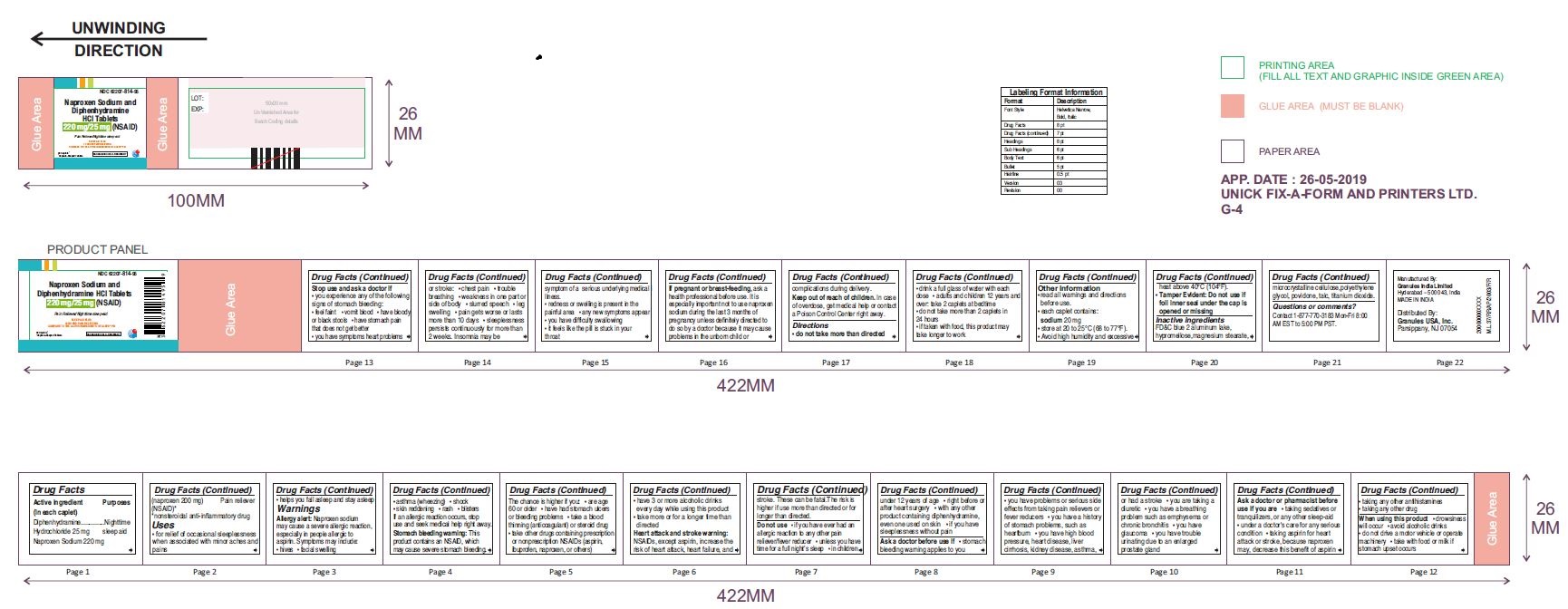 DRUG LABEL: Naproxen Sodium and Diphenhydramine HCl
NDC: 62207-814 | Form: TABLET, FILM COATED
Manufacturer: Granules India Ltd
Category: otc | Type: HUMAN OTC DRUG LABEL
Date: 20250801

ACTIVE INGREDIENTS: NAPROXEN SODIUM 220 mg/1 1; DIPHENHYDRAMINE HYDROCHLORIDE 25 mg/1 1
INACTIVE INGREDIENTS: HYPROMELLOSE 2910 (3 MPA.S); MAGNESIUM STEARATE; MICROCRYSTALLINE CELLULOSE; POLYETHYLENE GLYCOL; POVIDONE; TALC; TITANIUM DIOXIDE; HYPROMELLOSE 2910 (6 MPA.S); FD&C BLUE NO. 2--ALUMINUM LAKE

Naproxen Sodium and Diphenhydramaine HCl Tablets

ACTIVE INGREDIENT(S)

Diphenhydramine Hydrochloride 25 mg
Naproxen Sodium 220 mg (naproxen 200 mg) (NSAID)*
* nonsteroidal anti-inflammatory drug

PURPOSE

Night time sleep aid
Pain reliever

USE(S)

- for relief of occasional sleeplessness when associated with minor aches and pains
- helps you fall asleep and stay asleep

WARNINGS

Allergy alert:
Naproxen sodium may cause a severe allergic reaction, especially in people allergic to aspirin. Symptoms may include:
• hives
• facial swelling
• asthma(wheezing)
• shock
• skin reddening
• rash
• blisters
If an allergic reaction occurs, stop use and seek medical help right away.
Stomach bleeding warning:
This product contains an NSAID, which may cause severe stomach bleeding. The chance is higher if you:
• are age 60 or older
• have had stomach ulcers or bleeding problems
• take a blood thinning (anticoagulant) or steroid drug
• take other drugs containing prescription or nonprescription NSAIDs (aspirin, ibuprofen, naproxen, or others)
• have 3 or more alcoholic drinks every day while using this product
• take more or for a longer time than directed
Heart attack and stroke warning:
NSAIDs, except aspirin, increase the risk of heart attack, heart failure, and stroke. These can be fatal. The risk is higher if use more than directed or for longer than directed.

DO NOT USE

• if you have ever had an allergic reaction to any other pain reliever/fever reducer
• unless you have time for a full night’s sleep
• in children under 12 years of age
• right before or after heart surgery
• with any other product containing diphenhydramine, even one used on skin
• if you have sleeplessness without pain

ASK A DOCTOR BEFORE USE IF

• stomach bleeding warning applies to you
• you have problems or serious side effects from taking pain relievers or fever reducers
• you have a history of stomach problems, such as heartburn
• you have high blood pressure, heart disease, liver cirrhosis, kidney disease, asthma, Drug Facts Drug Facts or had a stroke
• you are taking a diuretic
• you have a breathing problem such as emphysema or chronic bronchitis
• you have glaucoma
• you have trouble urinating due to an enlarged prostate gland

ASK A DOCTOR OR PHARMACIST BEFORE USE IF

• taking sedatives or tranquilizers, or any other sleep-aid
• under a doctor's care for any serious condition
• taking aspirin for heart attack or stroke, because naproxen may, decrease this benefit of aspirin
• taking any other antihistamines
• taking any other drug

WHEN USING THIS PRODUCT

• drowsiness will occur
• avoid alcoholic drinks
• do not drive a motor vehicle or operate machinery
• take with food or milk if stomach upset occurs

STOP USE AND ASK DOCTOR IF

• you experience any of the following signs of stomach bleeding:
• feel faint
• vomit blood
• have bloody or black stools
• have stomach pain that does not get better
• you have symptoms heart problems or stroke:
• chest pain
• trouble breathing
• weakness in one part or side of body
• slurred speech
• leg swelling
• pain gets worse or lasts more than 10 days
• sleeplessness persists continuously for more than 2 weeks. Insomnia may be symptom of a serious underlying medical illness.
• redness or swelling is present in the painful area
• any new symptoms appear
• you have difficulty swallowing
• it feels like the pill is stuck in your throat

IF PREGNANT OR BREASTFEEDING

ask a health professional before use. It is especially important not to use naproxen sodium during the last 3 months of pregnancy unless definitely directed to do so by a doctor because it may cause problems in the unborn child or complications during delivery.

KEEP OUT OF REACH OF CHILDREN

In case of overdose, get medical help or contact a Poison Control Center right away.

DIRECTIONS

• do not take more than directed
• drink a full glass of water with each dose
• adults and children 12 years and over: take 2 caplets at bedtime
• do not take more than 2 caplets in 24 hours
• if taken with food, this product may take longer to work

OTHER INFORMATION

• read all warnings and directions before use.

• each caplet contains: sodium 20 mg
• store at 20 to 25°C (68 to 77°F).
• avoid high humidity and excessive heat above 40°C (104°F).

- Tamper Evident: Do not use if foil inner seal under the cap is opened or missing

INACTIVE INGREDIENTS

FD&C blue2 aluminum lake, hypromellose, magnesiumstearate, microcrystalline cellulose, polyethyleneglycol, povidone, talc, titanium dioxide.

QUESTIONS OR COMMENTS ?

Contact 1-877-770-3183
Mon-Fri 8:00 AM EST to 5:00 PM PST.

PRINCIPAL DISPLAY PANEL

Naproxen Sodium and
Diphenhydramine HCl Tablets
220 mg/25 mg (NSAID)
Pain Reliever/Nighttime sleep-aid

SLEEP AID PLUS

12 HOUR PAIN RELIEVING

COMPARE TO THE ACTIVE INGREDIENTS OF ALEVE PM

20 Caplets†

†Capsule-Shaped Tablets

PRINCIPAL DISPLAY PANEL

Naproxen Sodium and
Diphenhydramine HCl Tablets
220 mg/25 mg (NSAID)
Pain Reliever/Nighttime sleep-aid

SLEEP AID PLUS

12 HOUR PAIN RELIEVING

COMPARE TO THE ACTIVE INGREDIENTS OF ALEVE PM

500 Caplets†

†Capsule-Shaped Tablets